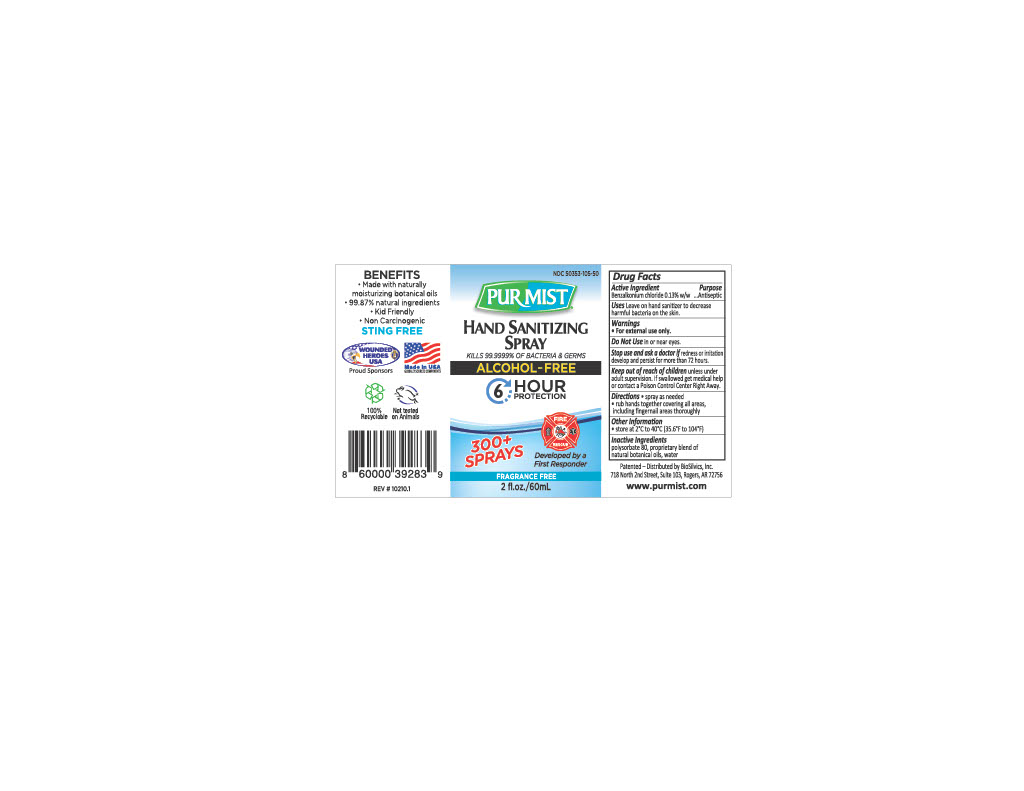 DRUG LABEL: Purmist
NDC: 50353-105 | Form: LIQUID
Manufacturer: MKR International Inc
Category: otc | Type: HUMAN OTC DRUG LABEL
Date: 20220407

ACTIVE INGREDIENTS: BENZALKONIUM CHLORIDE 0.13 g/1 mL
INACTIVE INGREDIENTS: POLYSORBATE 80; WATER

Hand Sanitizer

Active Ingredient

Benzalkonium Cl 0.13%

Purpose

Antiseptic

Uses

Leave on hand sanitizer to decrease harmful bacteria on the skin.

Warnings

For external use only.

DO NOT USE

in or near eyes.

Stop use and ask a doctor if

redness or irritation develop or persist for more than 72 hours.

Keep out of reach of children

unless under adult supervision. If swallowed get medical help or contact a Poison Control Center right away.

Directions

- Spray as neeeded
- Rub hands together covering all areas, including fingernail areas thoroughly

Other Information

store at 2ºC to 40ºC (35.6ºF to 104ºF)

Inactive Ingredients

polysorbate 80, proprietary blend of natural botanical oils, water

Indications and Usage

Leave on hand sanitizer to decrease harmful bacteria on the skin.

Dosage & Administration

300+ Sprays